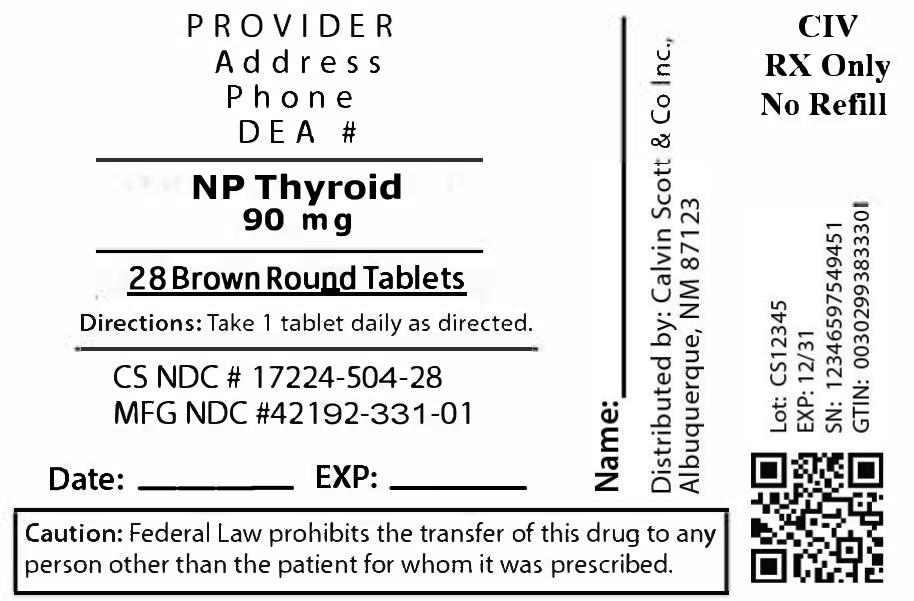 DRUG LABEL: NP Thyroid
NDC: 17224-504 | Form: TABLET
Manufacturer: Calvin Scott & Co Inc.
Category: otc | Type: HUMAN OTC DRUG LABEL
Date: 20250808

ACTIVE INGREDIENTS: LIOTHYRONINE 13.5 ug/1 1; LEVOTHYROXINE 57 ug/1 1
INACTIVE INGREDIENTS: MINERAL OIL; MALTODEXTRIN; ANHYDROUS DEXTROSE; CALCIUM STEARATE

NDC 17224-504-28

Take 1 tablet daily on an empty stomach or as directed

NDC 17224-504-28

Do not exceed recommended dose. Keep out of reach of children.

17224-504-28

Calcium stearate, dextrose, maltodextrin, mineral oil, modified wheat starch

17224-504-28

Used as a thyroid hormone replacement for hypothyroidism.

17224-504-28

Thyroid hormone replacement

17224-504-28

Thyroid 90 mg

17224-504-28

Keep out of reach of children. In case of accidental overdose, contact a doctor or Poison Control Center immediately.

NDC 17224-504-28

Package label for NP Thyroid 90 mg tablets (28 tablets per bottle). Contains product name, dosage strength, NDC 17224-504-28, manufacturer/repacker name, and usage instructions as printed on the label.